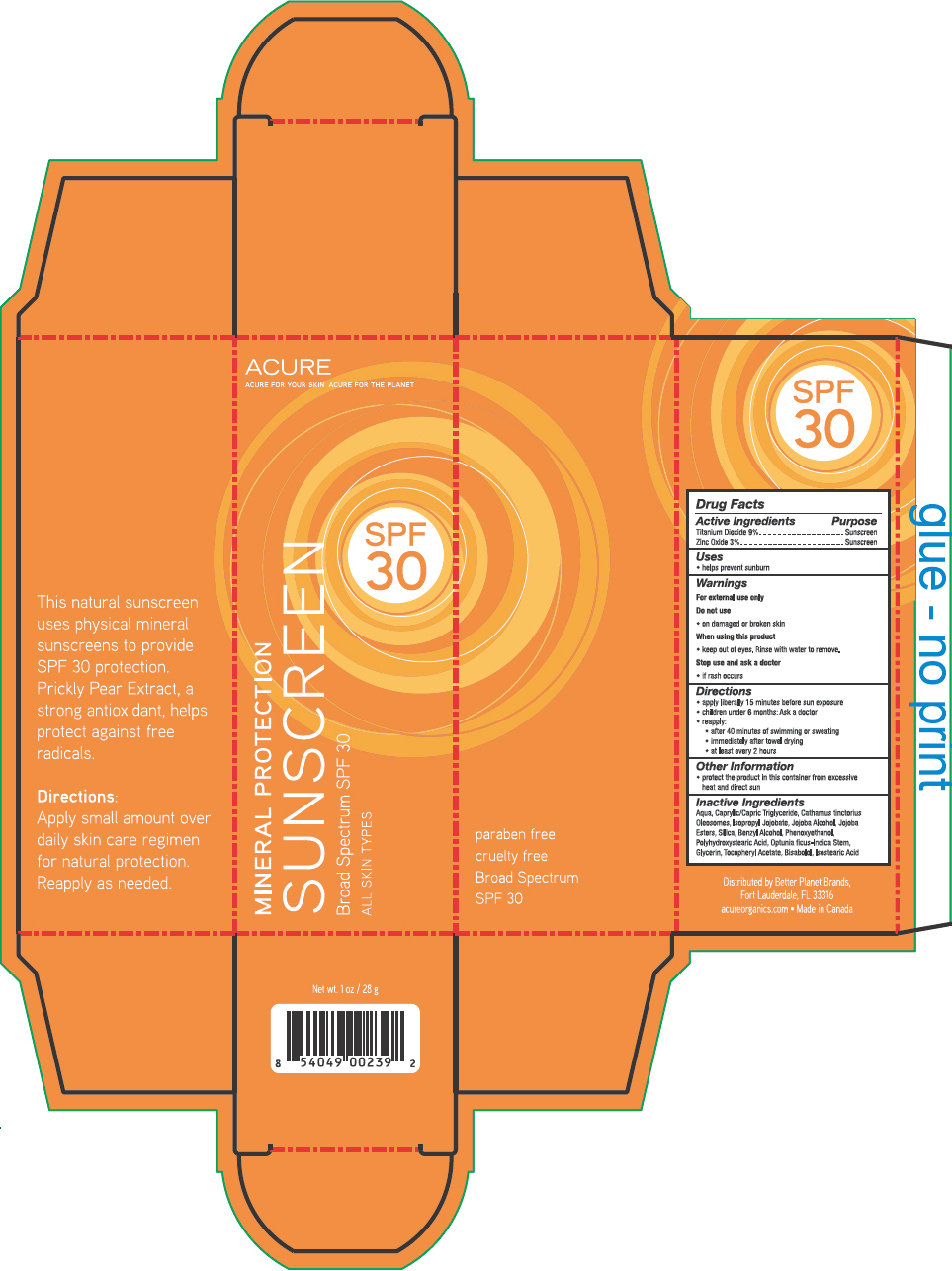 DRUG LABEL: Acure Mineral Protection Sunscreen Broad Spectrum SPF 30
NDC: 54136-030 | Form: LOTION
Manufacturer: Better Planet Brands
Category: otc | Type: HUMAN OTC DRUG LABEL
Date: 20121127

ACTIVE INGREDIENTS: TITANIUM DIOXIDE 9 g/100 g; ZINC OXIDE 3 g/100 g
INACTIVE INGREDIENTS: WATER; CAPRYLIC/CAPRIC MONO/DIGLYCERIDES; CARTHAMUS TINCTORIUS SEED OLEOSOMES; HYDROLYZED JOJOBA ESTERS (ACID FORM); SILICON DIOXIDE; BENZYL ALCOHOL; PHENOXYETHANOL; POLYHYDROXYSTEARIC ACID (2300 MW); GLYCERIN; OPUNTIA FICUS-INDICA; ALOE VERA LEAF; .ALPHA.-TOCOPHEROL ACETATE; LEVOMENOL; ALUMINUM STEARATE; ALUMINUM OXIDE; ISOSTEARIC ACID

Acure Mineral Protection Sunscreen Broad Spectrum SPF 30

Drug Facts

ACTIVE INGREDIENT

Active Ingredients | Purpose
Titanium Dioxide 9% | Sunscreen
Zinc Oxide 3% | Sunscreen

Uses

- helps prevent sunburn

Warnings

For external use only

Do not use

- on damaged or broken skin

When using this product

- keep out of eyes. Rinse with water to remove.

Stop use and ask a doctor

- if rash occurs

Directions

- apply liberally 15 minutes before sun exposure
- children under 6 months: Ask a doctor
- reapply:
  - after 40 minutes of swimming or sweating
  - immediately after towel drying
  - at least every 2 hours

Other Information

- protect the product in this container from excessive heat and direct sun

Inactive Ingredients

Aqua, Caprylic/Capric Triglyceride, Cathamus tinctorius Oleosomes, Isopropyl Jojobate, Jojoba Alcohol, Jojoba Esters, Silica, Benzyl Alcohol, Phenoxyethanol, Polyhydroxystearic Acid, Optunia ficus-Indica Stem, Glycerin, Tocopheryl Acetate, Bisabolol, Isostearic Acid

Distributed by Better Planet Brands,
Fort Lauderdale, FL 33316

PRINCIPAL DISPLAY PANEL - 28 g Tube Box

ACURE
ACURE FOR YOUR SKIN ACURE FOR THE PLANET

MINERAL PROTECTION
SUNSCREEN
Broad Spectrum SPF 30
ALL SKIN TYPES

SPF
30